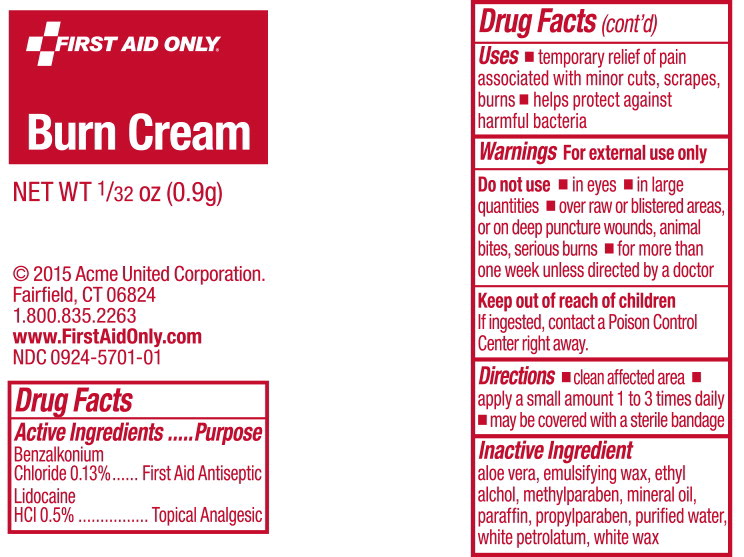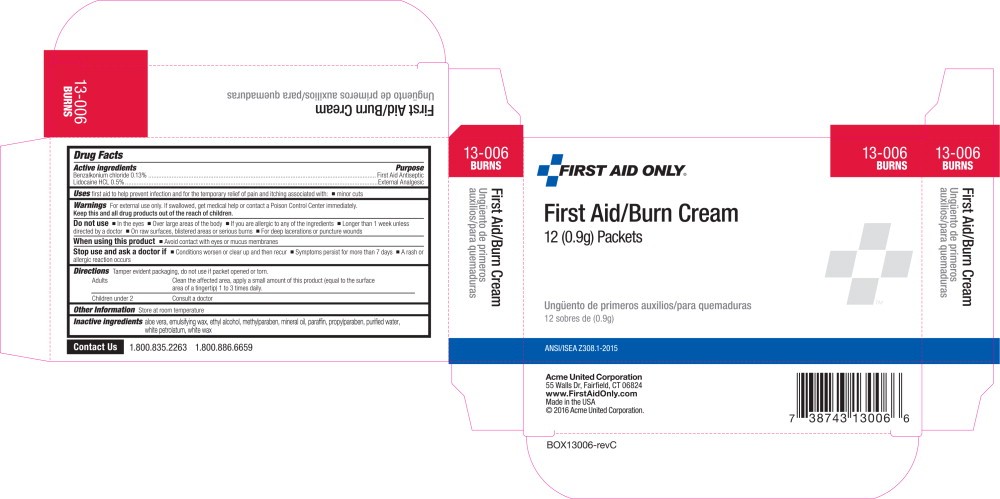 DRUG LABEL: First Aid and Burn
NDC: 0924-5701 | Form: CREAM
Manufacturer: Acme United Corporation
Category: otc | Type: HUMAN OTC DRUG LABEL
Date: 20160309

ACTIVE INGREDIENTS: benzalkonium chloride 1.3 mg/1 g; lidocaine hydrochloride 5 mg/1 g
INACTIVE INGREDIENTS: aloe vera leaf; alcohol; methylparaben; mineral oil; paraffin; propylparaben; water; petrolatum; white wax

Drug Facts

Active Ingredients

Benzalkonium Chloride 0.13%

Lidocaine HCl 0.5%

Purpose

First Aid Antiseptic

External analgesic

Uses

first aid to help prevent infection and for the temporary relief of itching associated with

- minor cuts
- scrapes
- burns

Warnings

For external use only

Do not use

- in the eyes or apply over large areas of the body
- longer than 1 week unless directed by a doctor
- in large quantities, particularly over raw surfaces or blistered areas

Ask a doctor before use if you have deep or puncture wounds, animal bites, or serious burns

When using this product avoid contact with eyes

Stop use and ask a doctor if

- condition worsens or persists for more than 7 days
- clears up and occurs again within a few days

Keep out of reach of children If swallowed, get medical help or contact a Poison Control Center right away.

Directions

- adults and children 2 years of age and older:
- clean the affected area
- apply a small amount of this product to the area 1 to 3 times daily
- may be covered with a sterile bandage
- children under 2 years of age: consult a doctor

Other information

- store at room temperature
- do not use if packet is opened or torn

Inactive ingredients

aloe vera, emulsifying wax, ethyl alcohol, methylparaben, mineral oil, paraffin, propylparaben, purified water, white petrolatum, white wax

Questions? 1-800-835-2263

REORDER
www.PhysiciansCareFirstAid.com
1 800 835 2263

Principal Display Panel - Packet Label

FIRST AID ONLY®

Burn Cream

NET WT 1/32 oz (0.9g)

© 2015 Acme United Corporation.

Faifield, CT 06824

1.800.835.2263

www.FirstAidOnly.com

NDC 0924-5701-01

Principal Display Panel - Packet Label

FIRST AID ONLY®

13-006

BURNS

First Aid/Burn Cream

12 (0.9g) Packets

Ungüento de primeros auxilios/para quemaduras

12 sobres de (0.9g)

NDC 0924-5701-10